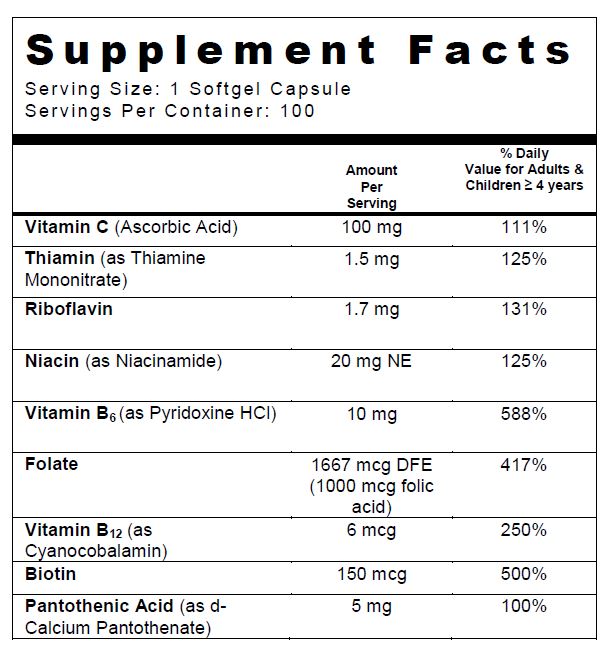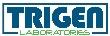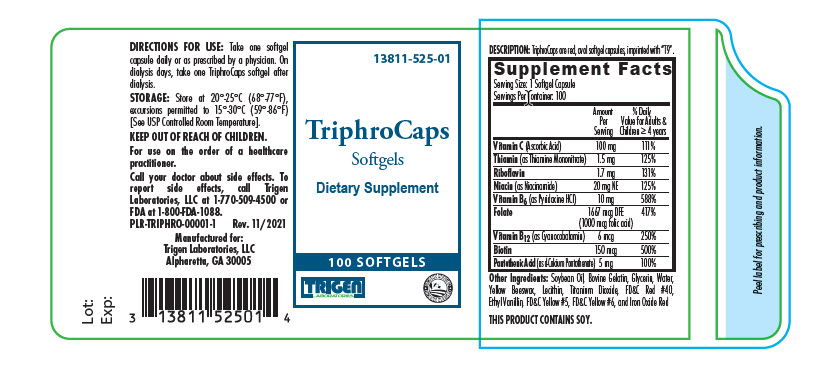 DRUG LABEL: TriphroCaps
NDC: 13811-525 | Form: CAPSULE
Manufacturer: Trigen Laboratories, LLC
Category: other | Type: DIETARY SUPPLEMENT
Date: 20211124

ACTIVE INGREDIENTS: folic acid 1 mg/1 1; ascorbic acid 100 mg/1 1; niacinamide 20 mg/1 1; thiamine mononitrate 1.5 mg/1 1; riboflavin 1.7 mg/1 1; pyridoxine Hydrochloride 10 mg/1 1; cyanocobalamin 6 ug/1 1; calcium pantothenate 5 mg/1 1; biotin 150 ug/1 1
INACTIVE INGREDIENTS: soybean oil; GELATIN TYPE B BOVINE (160 BLOOM); glycerin; water; yellow wax; titanium dioxide; FD&C Red No. 40; ethyl vanillin; FD&C yellow No. 5; FD&C yellow No. 6; ferric oxide red; LECITHIN, SOYBEAN

TriphroCaps
Softgels

SUPPLEMENT FACTS

Other Ingredients: Soybean Oil, Bovine Gelatin, Glycerin, Water, Yellow Beeswax, Lecithin, Titanium Dioxide, FD&C Red #40, Ethyl Vanillin, FD&C Yellow #5, FD&C Yellow #6, and Iron Oxide Red

THIS PRODUCT CONTAINS SOY.

TriphroCaps are an orally administered prescription vitamin used for the dietary management of patients with nutritional deficiencies or are in need of nutritional supplementation.

CONTRAINDICATIONS

TriphroCaps are contraindicated in patients with a known hypersensitivity to any of the ingredients including soy.

PRECAUTIONS

Folic acid alone is an improper therapy in the treatment of pernicious anemia and other megaloblastic anemias where Vitamin B12 is deficient. Folic acid in doses above 0.1 mg daily may obscure pernicious anemia in that hematologic remission can occur while neurological manifestations remain progressive.

The patient’s medical conditions and consumption of other drugs, herbs, and/or supplements should be considered.

Pediatric Use: Safety and effectiveness in pediatric patients have not been established.

Geriatric Use: Safety and effectiveness in elderly patients have not been established.

Biotin levels higher than the recommended daily allowance may cause interference with some laboratory tests, including cardiovascular diagnostic tests (e.g. troponin) and hormone tests, and may lead to incorrect test results. Tell your healthcare provider about all prescription and over-the-counter medicines, vitamins, and dietary supplements that you take, including biotin.

This product contains FD&C Yellow No. 5 (tartrazine) which may cause allergic-type reactions (including bronchial asthma) in certain susceptible patients. Although the overall incidence of FD&C Yellow No. 5 (tartrazine) sensitivity in the general population is low, it is frequently seen in patients who also have aspirin hypersensitivity.

DRUG INTERACTIONS

TriphroCaps is not recommended for and should not be given to patients receiving levodopa because the action of levodopa is antagonized by pyridoxine. There is a possibility of increased bleeding due to pyridoxine interaction with anticoagulants (e.g., Aspirin, Heparin, Clopidogrel).

ADVERSE REACTIONS

Allergic sensitization has been reported following both oral and parenteral administration of folic acid.

DESCRIPTION

TriphroCaps are red, oval softgel capsules, imprinted with "T9".

DIRECTIONS FOR USE

Take one softgel capsule daily or as prescribed by a physician. On dialysis days, take one TriphroCaps softgel after dialysis.

HOW SUPPLIED

TriphroCaps are supplied in bottles of 100 softgel capsules.

Product Code: 13811-525-01

STORAGE

Store at 20°-25°C (68°-77°F), excursions permitted to 15°-30°C (59°-86°F) [See USP Controlled Room Temperature].

KEEP OUT OF REACH OF CHILDREN.

For use on the order of a healthcare practitioner.

Call your doctor about side effects. To report side effects, call Trigen Laboratories, LLC at 1-770-509-4500 or FDA at 1-800-FDA-1088.

PLR-TRIPHRO-00001-1 Rev. 11/2021

Manufactured for:

Trigen Laboratories, LLC

Alpharetta, GA 30005

PRINCIPAL DISPLAY PANEL - 100 Softgel Bottle Label

13811-525-01

TriphroCaps
Softgels

100 SOFTGELS

TRIGEN
LABORATORIES